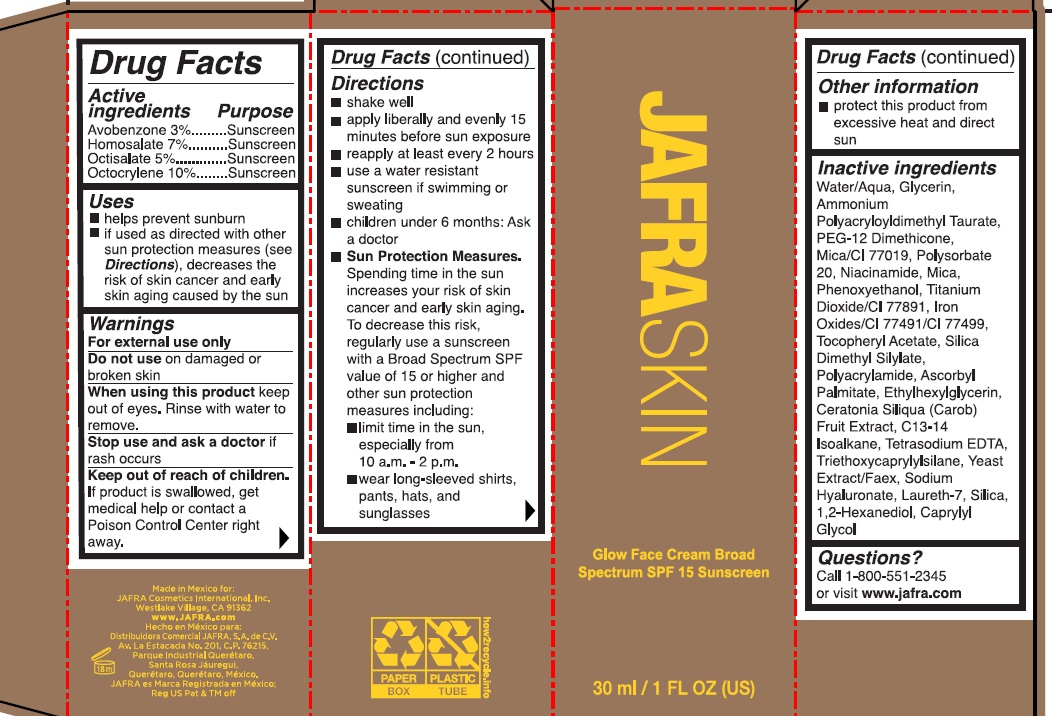 DRUG LABEL: JAFRA SKIN Glow Face Cream Broad Spectrum SPF 15 Sunscreen
NDC: 68828-021 | Form: CREAM
Manufacturer: Distribuidora Comercial Jafra, S.A. de C.V
Category: otc | Type: HUMAN OTC DRUG LABEL
Date: 20250117

ACTIVE INGREDIENTS: AVOBENZONE 3 g/100 mL; HOMOSALATE 7 g/100 mL; OCTISALATE 5 g/100 mL; OCTOCRYLENE 10 g/100 mL
INACTIVE INGREDIENTS: WATER; GLYCERIN; AMMONIUM POLYACRYLOYLDIMETHYL TAURATE; PEG-12 DIMETHICONE (300 CST); MICA; POLYSORBATE 20; NIACINAMIDE; PHENOXYETHANOL; TITANIUM DIOXIDE; FERRIC OXIDE RED; FERROSOFERRIC OXIDE; .ALPHA.-TOCOPHEROL ACETATE; SILICA DIMETHYL SILYLATE; SODIUM ACRYLOYLDIMETHYLTAURATE-ACRYLAMIDE COPOLYMER (1:1; 90000-150000 MPA.S); ASCORBYL PALMITATE; ETHYLHEXYLGLYCERIN; CAROB; C13-14 ISOPARAFFIN; EDETATE SODIUM; TRIETHOXYCAPRYLYLSILANE; YEAST, UNSPECIFIED; HYALURONATE SODIUM; LAURETH-7; SILICON DIOXIDE; 1,2-HEXANEDIOL; CAPRYLYL GLYCOL

JAFRA SKIN GLOW FACE CREAM BROAD SPECTRUM SPF 15 SUNSCREEN

Active Ingredients Purpose

Avobenzone 3% Sunscreen

Homosalate 7% Sunscreen

Octisalate 5% Sunscreen

Octocrylene 10% Sunscreen

Uses

- helps prevent sunburn
- if used as directed with other sun protection measures (see Directions), decreases the risk of skin cancer and early skin aging caused by the sun

Warnings

For external use only

Do not use ondamaged or broken skin

When using this productkeep out of eyes. Rinse with water to remove

Stop use and ask a doctorif rash occurs

Keep out of reach of children. If product is swallowed, get medical help or contact a Poison Control Center right away.

Directions

- shake well
- apply liberally and evenly 15 minutes before sun exposure
- reapply at least every 2 hours
- use a water resistant sunscreen if swimming or sweating
- children under 6 months: Ask a doctor
- Sun Protection measures. Spending time in the sun increases your risk of skin cancer and early skin aging. To decrease this risk, regularly use a sunscreen with a Broad Spectrum SPF value of 15 or higher and other sun protection measures including:
- limit time in the sun, especially from 10 a.m.-2 p.m.
- Wear long-sleeved shirts, pants, hats, and sunglasses

Other information

- protect this product from excessive heat and direct sun

Inactive Ingredients

Water/Aqua, Glycerin, Ammonium Polyacryloyldimethyl Taurate, PEG-12 Dimethicone, Mica/CI 77019, Polysorbate 20, Niacinamide, Mica, Phenoxyethanol, Titanium Dioxide/CI 77891, Iron Oxides/CI 77491/CI 77499, Tocopheryl Acetate, Silica Dimethyl Silylate, Polyacrylamide, Ascorbyl Palmitate, Ethylhexylglycerin, Ceratonia Siliqua (Carob) Fruit Extract, C13-14 Isoalkane, Tetrasodium EDTA, Triethoxycaprylylsilane, Yeast Extract/Faex, Sodium Hyaluronate, Laureth-7, Silica, 1,2-Hexanediol, Caprylyl Glycol

Questions?

Call 1-800-551-2345 or visit www.jafra.com